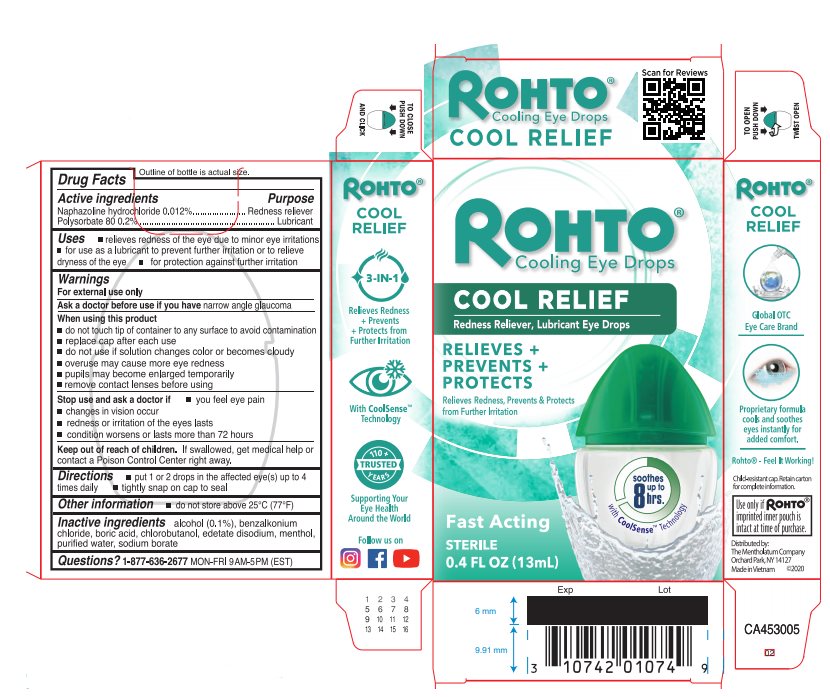 DRUG LABEL: Rohto
NDC: 10742-8141 | Form: LIQUID
Manufacturer: The Mentholatum Company
Category: otc | Type: HUMAN OTC DRUG LABEL
Date: 20241217

ACTIVE INGREDIENTS: NAPHAZOLINE HYDROCHLORIDE 0.12 mg/1 mL; POLYSORBATE 80 2 mg/1 mL
INACTIVE INGREDIENTS: ALCOHOL 1 mg/1 mL; BENZALKONIUM CHLORIDE; BORIC ACID; CHLOROBUTANOL; EDETATE DISODIUM; MENTHOL, UNSPECIFIED FORM; WATER; SODIUM BORATE

Drug Facts

Active ingredients

Naphazoline hydrochloride 0.012%

Polysorbate 80 0.2%

Purpose

Naphazoline hydrochloride - Redness reliever

Polysorbate 80 - Lubricant

Uses

- relieves redness of the eye due to minor eye irritations
- for use as a lubricant to prevent further irritation or to relieve dryness of the eye
- for protection against further irritation

Warnings

For external use only

Ask a doctor before use if you have

narrow angle glaucoma

When using this product

- do not touch tip of container to any surface to avoid contamination
- replace cap after each use
- do not use if solution changes color or becomes cloudy
- overuse may cause more eye redness
- pupils may become enlarged temporarily
- remove contact lenses before using

Stop use and ask a doctor if

- you feel eye pain
- changes in vision occur
- redness or irritation of the eyes lasts
- condition worsens or lasts more than 72 hours

Keep out of reach of children.

If swallowed, get medical help or contact a Poison Control Center right away.

Directions

- put 1 or 2 drops in the affected eye(s) up to 4 times daily
- tightly snap on cap to seal

Other information

- do not store above 25°C (77°F)

Inactive ingredients

alcohol (0.1%), benzalkonium chloride, boric acid, chlorobutanol, edetate disodium, menthol, purified water, sodium borate

Questions?

1-877-636-2677 MON-FRI 9 AM - 5 PM (EST)